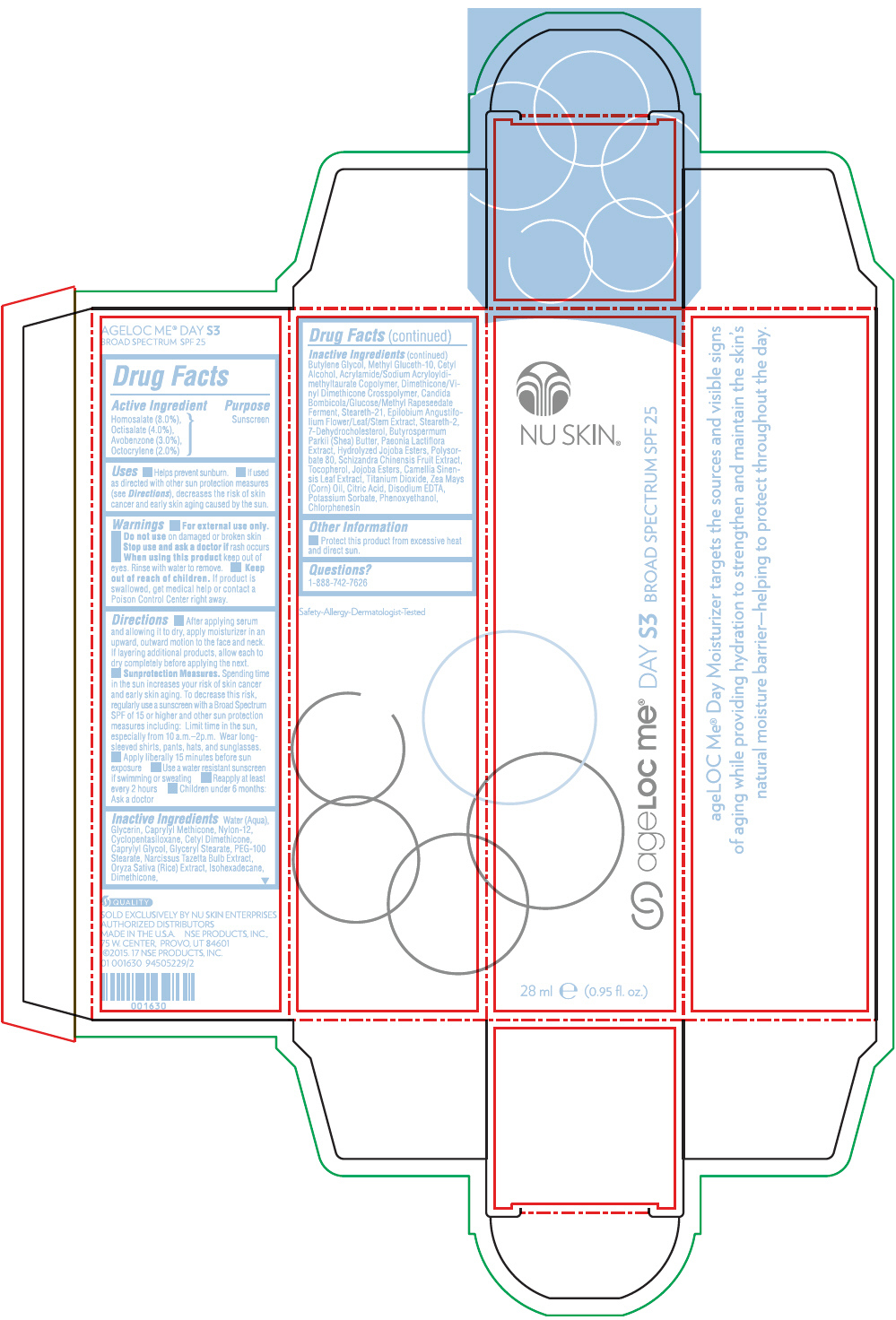 DRUG LABEL: Nu Skin ageLOC Me Day S3 Broad Spectrum SPF 25
NDC: 62839-1630 | Form: LOTION
Manufacturer: NSE Products, Inc.
Category: otc | Type: HUMAN OTC DRUG LABEL
Date: 20241226

ACTIVE INGREDIENTS: Homosalate 80 mg/1 mL; Octisalate 40 mg/1 mL; Avobenzone 30 mg/1 mL; Octocrylene 20 mg/1 mL
INACTIVE INGREDIENTS: Water; Glycerin; Caprylyl Trisiloxane; Nylon-12; Cyclomethicone 5; Caprylyl Glycol; Glyceryl Monostearate; PEG-100 Stearate; Cetyl Alcohol; Methyl Gluceth-10; Steareth-2; Steareth-21; Isohexadecane; Dimethicone; Butylene Glycol; Rice Germ; Phenoxyethanol; Chlorphenesin; Hydrolyzed Jojoba Esters (Acid Form); Polysorbate 80; Shea Butter; Titanium Dioxide; Edetate Disodium; Green Tea Leaf; Epilobium Angustifolium Flowering Top; Citric Acid Monohydrate; Schisandra Chinensis Fruit; Corn Oil; Potassium Sorbate; Narcissus Tazetta Bulb; 7-Dehydrocholesterol; Tocopherol

Nu Skin® ageLOC Me® Day S3 Broad Spectrum SPF 25

Drug Facts

Active Ingredient

Homosalate (8.0%),
Octisalate (4.0%),
Avobenzone (3.0%),
Octocrylene (2.0%)

Purpose

Sunscreen

Uses

- Helps prevent sunburn.
- If used as directed with other sun protection measures (see Directions), decreases the risk of skin cancer and early skin aging caused by the sun.

Warnings

- For external use only.

- Do not use on damaged or broken skin

- Stop use and ask a doctor if rash occurs

- When using this product keep out of eyes. Rinse with water to remove.

- Keep out of reach of children. If product is swallowed, get medical help or contact a Poison Control Center right away.

Directions

- After applying serum and allowing it to dry, apply moisturizer in an upward, outward motion to the face and neck. If layering additional products, allow each to dry completely before applying the next.
- Sunprotection Measures. Spending time in the sun increases your risk of skin cancer and early skin aging. To decrease this risk, regularly use a sunscreen with a Broad Spectrum SPF of 15 or higher and other sun protection measures including: Limit time in the sun, especially from 10 a.m.–2p.m. Wear long-sleeved shirts, pants, hats, and sunglasses.
- Apply liberally 15 minutes before sun exposure
- Use a water resistant sunscreen if swimming or sweating
- Reapply at least every 2 hours
- Children under 6 months: Ask a doctor

Inactive Ingredients

Water (Aqua), Glycerin, Caprylyl Methicone, Nylon-12, Cyclopentasiloxane, Cetyl Dimethicone, Caprylyl Glycol, Glyceryl Stearate, PEG-100 Stearate, Narcissus Tazetta Bulb Extract, Oryza Sativa (Rice) Extract, Isohexadecane, Dimethicone, Butylene Glycol, Methyl Gluceth-10, Cetyl Alcohol, Acrylamide/Sodium Acryloyldimethyltaurate Copolymer, Dimethicone/Vinyl Dimethicone Crosspolymer, Candida Bombicola/Glucose/Methyl Rapeseedate Ferment, Steareth-21, Epilobium Angustifolium Flower/Leaf/Stem Extract, Steareth-2, 7-Dehydrocholesterol, Butyrospermum Parkii (Shea) Butter, Paeonia Lactiflora Extract, Hydrolyzed Jojoba Esters, Polysorbate 80, Schizandra Chinensis Fruit Extract, Tocopherol, Jojoba Esters, Camellia Sinensis Leaf Extract, Titanium Dioxide, Zea Mays (Corn) Oil, Citric Acid, Disodium EDTA, Potassium Sorbate, Phenoxyethanol, Chlorphenesin

Other Information

- Protect this product from excessive heat and direct sun.

Questions?

1-888-742-7626

PRINCIPAL DISPLAY PANEL - 28 ml Cartridge Carton

NU SKIN®

ageLOC me® DAY S3 BROAD SPECTRUM SPF 25

28 ml e (0.95 fl. oz.)